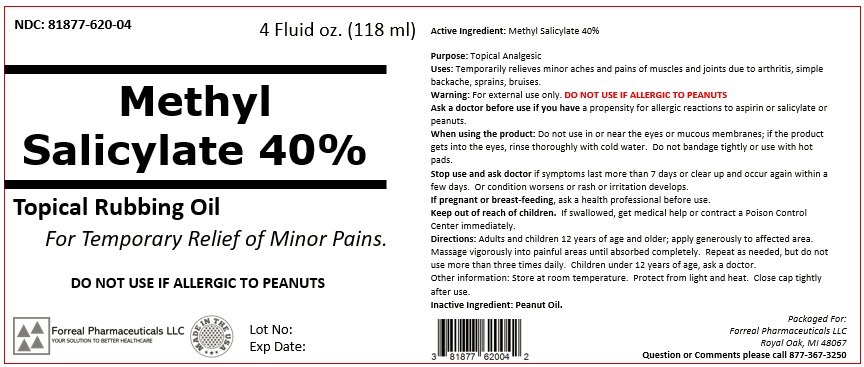 DRUG LABEL: Methyl Salicylate 40% Topical Oil
NDC: 81877-620 | Form: LIQUID
Manufacturer: FORREAL PHARMACEUTICALS LLC 
Category: otc | Type: HUMAN OTC DRUG LABEL
Date: 20251007

ACTIVE INGREDIENTS: METHYL SALICYLATE 40 g/100 mL
INACTIVE INGREDIENTS: PEANUT OIL

Active ingredient: Methyl Salicylate 40%

Purpose: Topical Analgesic

INDICATIONS AND USAGE

Uses: Temporarily relieves minor aches and pains of muscles and joints due to arthritis, simple backache, sprains, bruises.

WARNINGS

Warning: For external use only. DO NOT USE IF ALLERGIC TO PEANUTS

Ask a doctor before use if you have a propensity for allergic reactions to aspirin or salicylate or peanuts.

WHEN USING

When using the product: Do not use in or near the eyes or mucous membranes; if the product gets into the eyes, rinse thoroughly with cold water. Do not bandage tightly or use with hot pads.

Stop use and ask doctor if symptoms last more than 7 days or clear up and occur again within a few days. Or condition worsens or rash or irritation develops.

PREGNANCY OR BREAST FEEDING

If pregnant or breast-feeding, ask a health professional before use.

Keep out of reach of children. if swallowed, get medical help or contract a Poison Control Center immediately.

DOSAGE AND ADMINISTRATION

Directions: Adults and children 12 years of age and older; apply generously to affected area. Massage vigorously into painful areas until absorbed completely. Repeat as needed, but do not use more than three times daily. Children under 12 years of age, ask a doctor.
Other information: Store at room tempreature. Protect from light and heat. Close cap tightly after use.

Inactive ingredient: Peanut Oil.

Packaged For:
Forreal Pharmaceuticals LLC
Royal Oak, MI 48067
Question or Comments please call 877-367-3250

PRINCIPAL DISPLAY PANEL

NDC: 81877-620-04 4 Fluid oz. (118 ml)

Methyl
Salicylate 40%

Topical Rubbing Oil

For Temporary Relief of Minor Pains.

DO NOT USE IF ALLERGIC TO PEANUTS

Forreal Pharmaceuticals LLC
YOUR SOLUTION TO BETTER HEALTHCARE